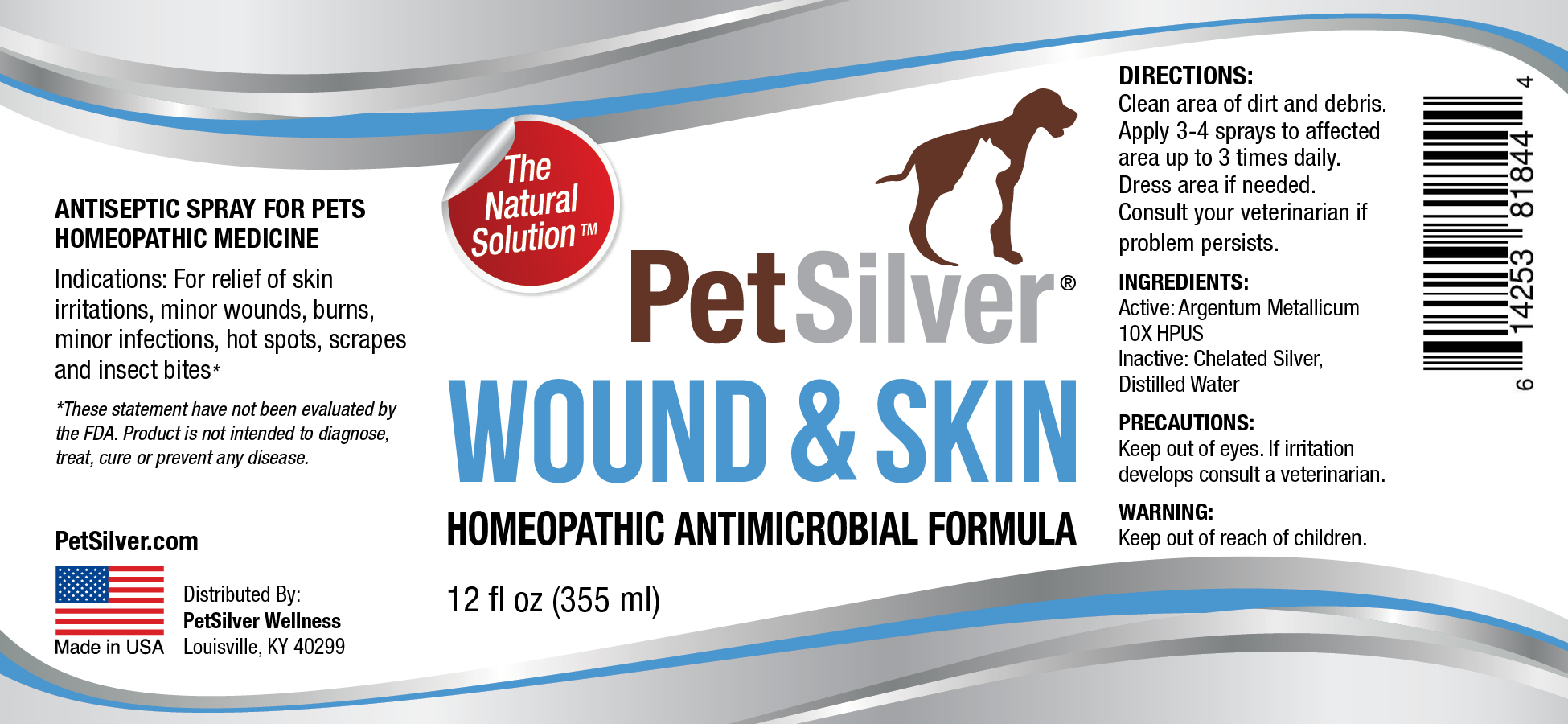 DRUG LABEL: Petsilver Wound 12
NDC: 72363-019 | Form: SPRAY
Manufacturer: AG Essence
Category: homeopathic | Type: HUMAN OTC DRUG LABEL
Date: 20251214

ACTIVE INGREDIENTS: SILVER 0.0105 g/355 g
INACTIVE INGREDIENTS: ANHYDROUS CITRIC ACID 0.054 g/355 g; WATER 353.9355 g/355 g

PetSilver Wound Spray 12

DIRECTIONS:

Clean area of dirt and debris. Apply 3-4 sprays to affected area up to 3 times daily. Dress area if needed. Consult your veterinarian if problem persists.

PRECAUTIONS:

Keep out of eyes. If irritation develops consult a veterinarian.

INGREDIENT:

Active: Argentum Metallicum10X HPUS

INGREDIENTS:

Inactive: Chelated Silver, Distilled Water

Indications

For relief of skin irritations, minor wounds, burns, minor infections, hot spots, scrapes and insect bites.

WARNING:

Keep out of reach of children.

WARNING:

Keep out reach of children